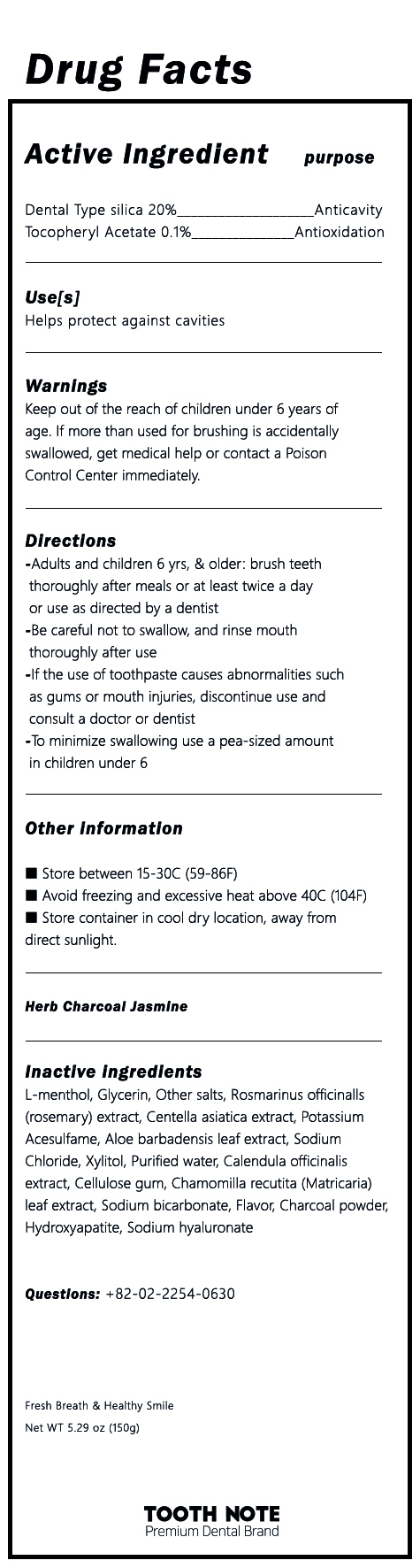 DRUG LABEL: TOOTH NOTE Herb Tooth Charcoal Jasmine
NDC: 81581-0003 | Form: PASTE, DENTIFRICE
Manufacturer: GI BILLIONS Co.,Ltd.	
Category: otc | Type: HUMAN OTC DRUG LABEL
Date: 20210224

ACTIVE INGREDIENTS: SILICON DIOXIDE 20 g/100 g; .ALPHA.-TOCOPHEROL ACETATE 0.1 g/100 g
INACTIVE INGREDIENTS: XYLITOL; WATER; LEVOMENTHOL; CENTELLA ASIATICA

ACTIVE INGREDIENT

Dental Type Silica, Tocopheryl Acetate

INACTIVE INGREDIENT

L-menthol, Other Salts, Rosmarinus Oficinalis (Rosemary) Extract, Centella asiatica extract, Potassium Acesulfame, Aloe barbadensis leaf extract, Glycerin, Sodium Chloride, Xylitol, Purified Water, Calendula officinalis extract, Cellulose gum, Chamomilla recutita (Matricaria) leaf extract, Sodium bicarbonate, Flavor, Charcoal Powder, Hydoxyapatite, Sodium hyaluronate

PURPOSE

Helps protect against cavities

Keep out of reach of children

INDICATIONS AND USAGE

Brush the teeth with an appropriate amount of toothpaste.

WARNINGS

1) Be careful not to swallow, and rinse mouth thoroughly after use
2) If the use of toothpaste causes abnormalities such as gums or mouth injuries, discontinue use and consult a doctor or dentist
3) If you are a child under 6 years of age, use a small amount of toothpaste as small as pea per use, and use under the supervision of a guardian to avoid sucking or swallowing
4 If a child under 6 years of age swallowed large quantities, consult a physician or dentist immediately
5) Keep out of the reach of children under 6 years

DOSAGE AND ADMINISTRATION

For dental use only